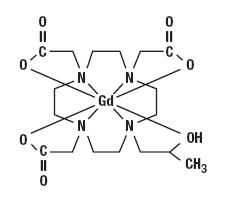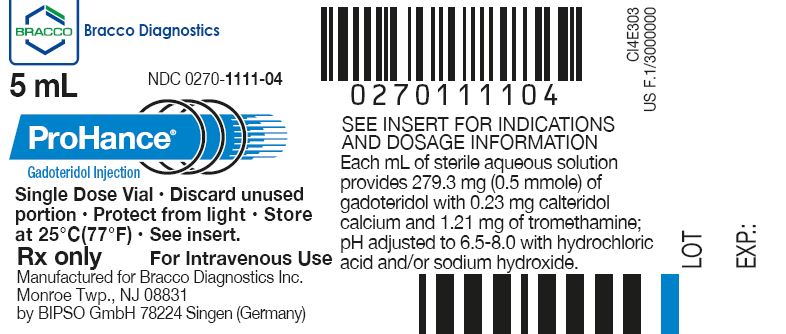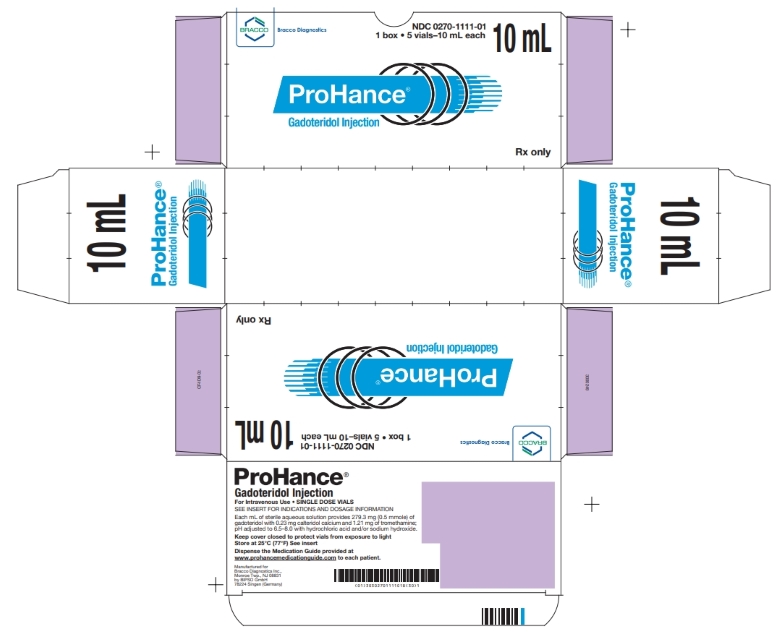 DRUG LABEL: ProHance
NDC: 0270-1111 | Form: INJECTION, SOLUTION
Manufacturer: BRACCO DIAGNOSTICS INC
Category: prescription | Type: HUMAN PRESCRIPTION DRUG LABEL
Date: 20250314

ACTIVE INGREDIENTS: gadoteridol 279.3 mg/1 mL
INACTIVE INGREDIENTS: calteridol calcium .23 mg/1 mL; tromethamine 1.21 mg/1 mL

HIGHLIGHTS OF PRESCRIBING INFORMATION

These highlights do not include all the information needed to use PROHANCE safely and effectively. See full prescribing information for PROHANCE.
PROHANCE (gadoteridol injection) single dose, for intravenous use
Initial U.S. Approval: 1992

WARNING: RISK ASSOCIATED WITH INTRATHECAL USE and NEPHROGENIC SYSTEMIC FIBROSIS

See full prescribing information for complete boxed warning

- Intrathecal administration of gadolinium based contrast agents (GBCAs) can cause serious adverse reactions including death, coma, encephalopathy, and seizures. ProHance is not approved for intrathecal use. (5.1)
- GBCAs increase the risk for nephrogenic systemic fibrosis (NSF) among patients with impaired elimination of the drugs. Avoid use of ProHance in these patients unless the diagnostic information is essential and not available with non-contrasted MRI or other modalities. NSF may result in fatal or debilitating systemic fibrosis affecting the skin, muscle and internal organs. The risk for NSF appears highest among patients with:
  - chronic, severe kidney disease (GFR less than 30 mL/min/1.73m^2), or
  - acute kidney injury
  Screen patients for acute kidney injury and other conditions that may reduce renal function. For patients at risk for chronically reduced renal function (e.g. age greater than 60 years, hypertension or diabetes), estimate the glomerular filtration rate (GFR) through laboratory testing (5.2).

1 INDICATIONS AND USAGE

ProHance is a gadolinium-based contrast agent indicated for magnetic resonance imaging (MRI) to visualize:

- lesions with disrupted blood brain barrier and/or abnormal vascularity in the brain (intracranial lesions), spine and associated tissues in adults and pediatric patients, including term neonates (1.1)
- lesions in the head and neck in adults (1.2)

2 DOSAGE AND ADMINISTRATION

- Recommended dose in adult and pediatric patients is 0.2 mL/kg (0.1 mmol/kg) body weight administered as rapid intravenous infusion or bolus (2.1)
- Follow injection with a saline flush of at least 5 mL normal saline (2.1)

3 DOSAGE FORMS AND STRENGTHS

Injection: contains 279.3 mg/mL (0.5 mmol/mL) of gadoteridol supplied in single dose vials or pre-filled syringes (2.3, 3, 16)

4 CONTRAINDICATIONS

Allergic or hypersensitivity reactions to ProHance (4)

5 WARNINGS AND PRECAUTIONS

- Hypersensitivity: anaphylactic/anaphylactoid reactions with cardiovascular, respiratory and cutaneous manifestations, ranging from mild to severe reactions including shock can occur. Monitor patients closely for need of emergency cardiorespiratory support (5.3).
- Gadolinium is retained for months or years in brain, bone, and other organs. (5.4)

6 ADVERSE REACTIONS

The most commonly reported adverse reactions are nausea and taste perversion with an incidence ≥ 0.9% (6.1)

To report SUSPECTED ADVERSE REACTIONS, Contact Bracco Diagnostics Inc. at 1-800-257-5181 or FDA at 1-800-FDA-1088 or www.fda.gov/medwatch

8 USE IN SPECIFIC POPULATIONS

Pregnancy: Use only if imaging is essential during pregnancy and cannot be delayed. (8.1)

FULL PRESCRIBING INFORMATION

WARNING: RISK ASSOCIATED WITH INTRATHECAL USE and NEPHROGENIC SYSTEMIC FIBROSIS

Risk Associated with Intrathecal Use
Intrathecal administration of gadolinium-based contrast agents (GBCAs) can cause serious adverse reactions including death, coma, encephalopathy, and seizures. ProHance is not approved for intrathecal use [see Warnings and Precautions (5.1)].

Nephrogenic Systemic Fibrosis
GBCAs increase the risk for nephrogenic systemic fibrosis (NSF) among patients with impaired elimination of the drugs. Avoid use of ProHance in these patients unless the diagnostic information is essential and not available with non- contrasted MRI or other modalities. NSF may result in fatal or debilitating systemic fibrosis affecting the skin, muscle and internal organs.

The risk for NSF appears highest among patients with:

- chronic, severe kidney disease (GFR less than 30 mL/min/1.73m^2), or
- acute kidney injury

Screen patients for acute kidney injury and other conditions that may reduce renal function. For patients at risk for chronically reduced renal function (e.g. age greater than 60 years, hypertension or diabetes), estimate the glomerular filtration rate (GFR) through laboratory testing.

For patients at highest risk for NSF, do not exceed the recommended ProHance dose and allow a sufficient period of time for elimination of the drug from the body prior to re-administration [see Warnings and Precautions (5.2)].

1 INDICATIONS AND USAGE

1.1 MRI of the Central Nervous System (CNS)

ProHance is indicated for magnetic resonance imaging (MRI) in adults and pediatric patients including term neonates to visualize lesions with disrupted blood brain barrier and/or abnormal vascularity in the brain (intracranial lesions), spine and associated tissues.

1.2 MRI of Extracranial/Extraspinal Head and Neck

ProHance is indicated for MRI in adults to visualize lesions in the head and neck.

2 DOSAGE AND ADMINISTRATION

2.1 Recommended Dose

The recommended dose for adult and pediatric patients, including term neonates, is 0.2 mL/kg (0.1 mmol/kg) administered as a rapid intravenous infusion (10 mL/min to 60 mL/min) or bolus (greater than 60 mL/min). Table 1 provides weight-adjusted recommended dose volumes.

Table 1: Recommended Volume of ProHance Injection by Body Weight
Body Weight (kg) | Volume to be Administered (mL)
2.5 | 0.5
5 | 1
10 | 2
20 | 4
30 | 6
40 | 8
50 | 10
60 | 12
70 | 14
80 | 16
90 | 18
100 | 20
110 | 22
120 | 24
130 | 26
140 | 28
150 | 30

MRI of the CNS in Adults:

- A supplementary dose of 0.4 mL/kg (0.2 mmol/kg) may be given up to 30 minutes after the first dose in adult patients with normal renal function suspected of having poorly visualized CNS lesions, in the presence of negative or equivocal scans
- The safety and efficacy of supplementary dosing have not been established in pediatric patients

2.2 Administration

- Visually inspect ProHance for particulate matter and discoloration prior to use
- Do not administer the solution if it is discolored or particulate matter is present
- Concurrent medications or parenteral nutrition should not be physically mixed with contrast agents and should not be administered in the same intravenous line because of the potential for chemical incompatibility
- Inject at least a 5 mL normal saline flush immediately after ProHance injection to ensure complete administration
- Imaging procedures should be completed within 1 hour
- ProHance vials are intended only for single-dose administration. Administer immediately after opening and discard any unused product

2.3 Directions for Use

Vials

- Draw ProHance into the syringe immediately before use. Do not pierce the rubber stopper more than once. Discard any unused vial contents.

ProHance single dose syringe*

- Screw the threaded tip of the plunger rod clockwise into the cartridge plunger and push forward a few millimeters to break any friction between the cartridge plunger and syringe barrel

- Holding syringe erect, unscrew the plastic tip cap from the tip of the syringe and attach either a sterile, disposable needle or tubing with a compatible Luer lock using a push-twist action (slip tip)
- Hold the syringe erect and push plunger forward until all of the air is evacuated and fluid either appears at the tip of the needle or the tubing is filled
- Following the usual aspiration procedure, complete the injection
- Inject at least a 5 mL normal saline flush immediately after ProHance injection to ensure complete administration
- Properly dispose of the syringe and any other materials used

*The syringe assembly is a HYPAK SCF® single dose syringe supplied by Becton Dickinson

3 DOSAGE FORMS AND STRENGTHS

ProHance is supplied as a sterile, non-pyrogenic, and colorless to slightly yellow solution available in single-dose vials or prefilled syringes. Each mL contains 279.3 mg (0.5 mmol/mL) of gadoteridol for injection.

4 CONTRAINDICATIONS

ProHance is contraindicated in patients with known allergic or hypersensitivity reactions to ProHance [see Warnings and Precautions (5.3)].

5 WARNINGS AND PRECAUTIONS

5.1 Risk Associated with Intrathecal Use

Intrathecal administration of GBCAs can cause serious adverse reactions including death, coma, encephalopathy, and seizures. The safety and effectiveness of ProHance have not been established with intrathecal use. ProHance is not approved for intrathecal use [see Dosage and Administration (2.1)].

5.2 Nephrogenic Systemic Fibrosis

GCBAs increase the risk for nephrogenic systemic fibrosis (NSF) among patients with impaired elimination of the drugs. Avoid use of ProHance among these patients unless the diagnostic information is essential and not available with non-contrast MRI or other modalities. The GBCA-associated NSF risk appears highest for patients with chronic, severe kidney disease (GFR less than 30 mL/min/1.73m^2) as well as patients with acute kidney injury. The risk appears lower for patients with chronic, moderate kidney disease (GFR 30- 59 mL/min/1.73m^2) and little, if any, for patients with chronic, mild kidney disease (GFR 60-89 mL/min/1.73m^2). NSF may result in fatal or debilitating fibrosis affecting the skin, muscle and internal organs. Report any diagnosis of NSF following ProHance administration to Bracco Diagnostics (1-800-257-5181) or FDA (1-800-FDA-1088 or www.fda.gov/medwatch).

Screen patients for acute kidney injury and other conditions that may reduce renal function. Features of acute kidney injury consist of rapid (over hours to days) and usually reversible decrease in kidney function, commonly in the setting of surgery, severe infection, injury or drug-induced kidney toxicity. Serum creatinine levels and estimated GFR may not reliably assess renal function in the setting of acute kidney injury. For patients at risk for chronically reduced renal function (for example, age greater than 60 years, diabetes mellitus or chronic hypertension), estimate the GFR through laboratory testing.

Among the factors that may increase the risk for NSF are repeated or higher than recommended doses of a GBCA and the degree of renal impairment at the time of exposure. Record the specific GBCA and the dose administered to a patient. For patients at highest risk for NSF, do not exceed the recommended ProHance dose and allow a sufficient period of time for elimination of the drug prior to re-administration. For patients receiving hemodialysis, physicians may consider the prompt initiation of hemodialysis following the administration of a GBCA in order to enhance the contrast agent’s elimination. The usefulness of hemodialysis in the prevention of NSF is unknown. [see Clinical Pharmacology (12)].

5.3 Hypersensitivity Reactions

Anaphylactic and anaphylactoid reactions have been reported, involving cardiovascular, respiratory, and/or cutaneous manifestations. Some patients experienced circulatory collapse and died. In most cases, initial symptoms occurred within minutes of ProHance administration and resolved with prompt emergency treatment.

Prior to ProHance administration, ensure the availability of trained personnel and medications to treat hypersensitivity reactions. Consider the risk for hypersensitivity reactions, especially in patients with a history of hypersensitivity reactions or a history of asthma or other allergic disorders. If such a reaction occurs, stop ProHance and immediately begin appropriate therapy. Observe patients for signs and symptoms of a hypersensitivity reaction during and for up to 2 hours after ProHance administration.

5.4 Gadolinium Retention

Gadolinium is retained for months or years in several organs. The highest concentrations (nanomoles per gram of tissue) have been identified in the bone, followed by other organs (e.g. brain, skin, kidney, liver, and spleen). The duration of retention also varies by tissue and is longest in bone. Linear GBCAs cause more retention than macrocyclic GBCAs. At equivalent doses, retention varies among the linear agents with Omniscan (gadodiamide) and Optimark (gadoversetamide) causing greater retention than other linear agents [Eovist (gadoxetate disodium), Magnevist (gadopentetate dimeglumine), MultiHance (gadobenate dimeglumine)]. Retention is lowest and similar among the macrocyclic GBCAs [Dotarem (gadoterate meglumine), Gadavist (gadobutrol), ProHance (gadoteridol)].

Consequences of gadolinium retention in the brain have not been established. Pathologic and clinical consequences of GBCA administration and retention in skin and other organs have been established in patients with impaired renal function [see Warnings and Precautions (5.2)]. There are rare reports of pathologic skin changes in patients with normal renal function. Adverse events involving multiple organ systems have been reported in patients with normal renal function without an established causal link to gadolinium retention [see Adverse Reactions (6.2)].

While clinical consequences of gadolinium retention have not been established in patients with normal renal function, certain patients might be at higher risk. These include patients requiring multiple lifetime doses, pregnant and pediatric patients, and patients with inflammatory conditions. Consider the retention characteristics of the agent when choosing a GBCA for these patients. Minimize repetitive GBCA imaging studies, particularly closely spaced studies when possible.

5.5 Acute Kidney Injury

In patients with chronically reduced renal function, acute kidney injury requiring dialysis has occurred with the use of GBCAs. The risk of acute kidney injury may increase with increasing dose of the contrast agent; administer the lowest dose necessary for adequate imaging.

6 ADVERSE REACTIONS

The following serious adverse reactions are discussed in greater detail in other sections of the prescribing information:

- Nephrogenic systemic fibrosis [see Boxed Warning and Warnings and Precautions (5.2)]
- Hypersensitivity reactions [see Contraindications (4) and Warnings and Precautions (5.3)]

6.1 Clinical Trials Experience

Because clinical trials are conducted under widely varying conditions, adverse reaction rates observed in the clinical trials of a drug cannot be directly compared to rates in the clinical trials of another drug and may not reflect the rates observed in practice.

The adverse events described in this section were observed in clinical trials involving 3174 subjects (including 2896 adults and 278 pediatric subjects ages 0 to 17 years) exposed to ProHance. Approximately 48% of the subjects were men and ethnic distribution was 78% Caucasian, 6% Black, 3% Hispanic, 6% Asian, and 2% other. In 5% of the subjects, race was not reported. Average age was 47 years (range from 1 day to 91 years) and the exposure ranged from 0.03 to 0.3 mmol/kg.

Overall, approximately 5.8% of subjects reported one or more adverse reactions during a follow-up period that ranged from 24 hours to 7 days after ProHance administration.

Table 2 lists adverse reactions that occurred in ≥ 0.4% subjects who received ProHance.
Table 2: More frequent adverse reactions in clinical trials
Reaction | Rate (%) N = 3174
Nausea | 1.4%
Dysgeusia | 0.9%
Headache | 0.7%
Dizziness | 0.4%
Urticaria | 0.4%

The following additional adverse events occurred in fewer than 0.4% of the subjects:
General disorders and administration site conditions: | Asthenia; chest discomfort, facial edema, feeling hot, injection site coldness, injection site erythema, injection site pain, injection site warmth, pain, pyrexia
Cardiac: | Angina pectoris, palpitations, atrio-ventricular block first degree
Ear and labyrinth disorders: | Ear discomfort, tinnitus
Eye disorders: | Eye pruritis, lacrimation increased
Gastrointestinal disorders: | Abdominal discomfort, abdominal pain, diarrhea, dry mouth, gingival pain, oral pruritis, swollen tongue, vomiting
Infections and infestations: | Gingivitis, rhinitis
Investigations: | Alanine aminotransferase increased, aspartate aminotransferase increased, blood chloride increased, blood pressure immeasurable, blood urea decreased, hemoglobin decreased, heart rate increased
Metabolism and nutrition disorders: | Decreased appetite, hypoglycemia
Musculoskeletal and connective tissue disorders: | Back pain, musculoskeletal stiffness
Nervous system disorders: | Formication, hypoesthesia, hypokinesia, lethargy, loss of consciousness, migraine, paresthesia, presyncope, seizure, syncope, taste disorder
Psychiatric disorders: | Anxiety, mental status changes
Respiratory, thoracic and mediastinal disorders: | Cough, dry throat, dyspnea, nasal discomfort, throat irritation
Skin and subcutaneous tissue disorders: | Hyperhidrosis, pruritis, rash, rash morbilliform
Vascular disorders: | Flushing, hypotension, peripheral coldness, vascular rupture, vasodilatation, vasospasm

6.2 Postmarketing Experience

The following adverse reactions have been identified during post approval use of ProHance or other GBCAs that were not observed in the clinical trials. Because these reactions are reported voluntarily from a population of uncertain size, it is not always possible to reliably estimate their frequency or establish a causal relationship to drug exposure.

The following adverse drug reactions have also been reported:
General Disorders and Administration Site Conditions: | Adverse events with variable onset and duration have been reported after GBCA administration [see Warnings and Precautions (5.4)]. These include fatigue, asthenia, pain syndromes, and heterogeneous clusters of symptoms in the neurological, cutaneous, and musculoskeletal systems.
Cardiac disorders: | Cardiac arrest, bradycardia, hypertension
Gastrointestinal disorders: | Acute pancreatitis with onset within 48 hours after GBCA administration
Immune system disorders: | Hypersensitivity/anaphylactoid reactions including cardiac arrest, cyanosis, pharyngeal edema, laryngospasm, bronchospasm, angioedema, cough, sneezing, conjunctivitis, eyelid edema, hyperhidrosis, urticaria [see Warnings and Precautions (5.3)].
Nervous system disorders: | Coma, loss of consciousness, vasovagal reaction, tremor
Respiratory, thoracic and mediastinal disorders: | Respiratory arrest, acute respiratory distress syndrome, pulmonary edema
Renal and urinary system disorders: | Acute renal failure *
* Cases of acute renal failure have been reported in patients with pre-existing severe renal impairment.

8 USE IN SPECIFIC POPULATIONS

8.1 Pregnancy

Risk Summary
GBCAs cross the placenta and result in fetal exposure and gadolinium retention. The human data on the association between GBCAs and adverse fetal outcomes are limited and inconclusive (see Data). Because of the potential risks of gadolinium to the fetus, use ProHance only if imaging is essential during pregnancy and cannot be delayed.

In animal reproduction studies in rats, gadoteridol doubled the incidence of post-implantation loss at up to 16 times the recommended human dose (RHD). There were no adverse developmental effects observed in rabbits with intravenous administration of gadoteridol during organogenesis at doses up to 19 times the recommended human dose of 0.1 mmol/kg (see Data).

The estimated background risk of major birth defects and miscarriage for the indicated population is unknown. All pregnancies have a background risk of birth defect, loss, or other adverse outcomes. In the U.S. general population, the estimated background risk of major birth defects and miscarriage in clinically recognized pregnancies is 2 to 4% and is 15 to 20%, respectively.

Data
Human Data
Contrast agent is visualized in the placenta and fetal tissues after maternal GBCA administration. Cohort studies and case reports on exposure to GBCAs during pregnancy have not reported a clear association between GBCAs and adverse effects in the exposed neonates. However, a retrospective cohort study, comparing pregnant women who had a GBCA MRI to pregnant women who did not have an MRI, reported a higher occurrence of stillbirths and neonatal deaths in the group receiving GBCA MRI. Limitations of this study include a lack of comparison with non-contrast MRI and lack of information about the maternal indication for MRI.

Animal Data
Gadolinium Retention
GBCAs administered to pregnant non-human primates (0.1 mmol/kg on gestational days 85 and 135) result in measurable gadolinium concentration in the offspring in bone, brain, skin, liver, kidney, and spleen for at least 7 months. GBCAs administered to pregnant mice (2 mmol/kg daily on gestational days 16 through 19) result in measurable gadolinium concentrations in the pups in bone, brain, kidney, liver, blood, muscle, and spleen at one-month postnatal age.

Reproductive Toxicology
Gadoteridol was administered in intravenous doses of 0, 0.375, 1.5, 6.0, and 10 mmol/kg/day [0.6, 2.4, 9.7, and 16 times the recommended human dose (RHD) based on body surface area (BSA)] to female rats from gestational day (GD)6 until GD17. Gadoteridol at 10 mmol/kg/day for 12 days during gestation doubled the incidence of post-implantation loss. When rats were administered 6.0 or 10.0 mmol/kg/day for 12 days, an increase in spontaneous locomotor activity was observed in the offspring. Pregnant rabbits were administered gadoteridol in intravenous doses of 0, 0.4, 1.5, and 6 mmol/kg/day (1.3, 4.8, and 19.4 times the RHD based on BSA) from GD6 to GD18. Gadoteridol increased the incidence of spontaneous abortion and early delivery in rabbits administered 6 mmol/kg/day for 13 days during gestation.

8.2 Lactation

Risk Summary
There are no data on the presence of gadoteridol in human milk, the effects on the breastfed infant, or the effects on milk production. However, published lactation data on other GBCAs indicate that 0.01 to 0.04% of the maternal gadolinium dose is present in breast milk and there is limited GBCA gastrointestinal absorption in the breast-fed infant. Gadoteridol is present in rat milk (see Data). The developmental and health benefits of breastfeeding should be considered along with the mother’s clinical need for ProHance and any potential adverse effects on the breastfed infant from ProHance or from the underlying maternal condition.

Data
ProHance excretion in the milk of lactating rats was evaluated at 30 minutes, 6 and 24 hours after intravenous administration of 0.1 mmol/kg of ^153Gd-gadoteridol to nursing mothers. Small amounts of compound were found in milk immediately after injection (0.14% of the ID), with the amount declining to a low level 24 hours after injection (<0.01% of the ID).

8.4 Pediatric Use

The safety and effectiveness of ProHance have been established for use with MRI to visualize lesions with abnormal blood brain barrier or abnormal vascularity of the brain, spine, and associated tissues in pediatric patients from birth, including term neonates, to 17 years of age. Pediatric use is based on evidence of effectiveness in adults and in 103 pediatric patients 2 years of age and older, in addition to experience in 125 pediatric patients birth to less than 2 years of age that supported extrapolation from adult data [see Clinical Studies (14)]. Adverse reactions in pediatric patients were similar to those reported in adults [see Adverse Reactions (6.1)].

The safety and efficacy of > 0.1 mmol/kg, and sequential and/or repeat procedures have not been studied in pediatric patients [see Indications and Usage (1) and Dosage and Administration (2)].

No case of NSF associated with ProHance or any other GBCA has been identified in pediatric patients ages 6 years and younger. Pharmacokinetic studies suggest that weight normalized clearance of ProHance is similar in pediatric patients and adults, including pediatric patients age younger than 2 years. Normal estimated GFR (eGFR) is around 30 mL/min/1.73m^2 at birth and increases to mature levels around 1 year of age, reflecting growth in both glomerular function and relative body surface area. Clinical studies in pediatric patients younger than 1 year of age have been conducted in patients with the following minimum eGRF; 59.37 mL/min/1.73m^2 (age just after birth to < 30 days), 118.84 mL/min/1.73m^2 (age 30 days to < 6 months), 140.44 mL/min/1.73m^2 (age 6 to 12 months).

8.5 Geriatric Use

Of the total number of 2673 adult subjects in clinical studies of ProHance, 22% were 65 and over. No overall differences in safety were observed between these elderly subjects and the younger subjects.

ProHance is known to be substantially excreted by the kidneys, and the risk of toxic reactions from ProHance may be greater in patients with impaired renal function. Because elderly patients are more likely to have decreased renal function, it may be useful to monitor renal function.

8.6 Renal Impairment

No ProHance dosage adjustment is recommended for patients with renal impairment. Gadoteridol can be removed from the body by hemodialysis [see Warning and Precautions (5.2) and Clinical Pharmacology (12.3)].

10 OVERDOSAGE

Clinical consequences of overdose with ProHance have not been reported. The safety of ProHance has been tested in clinical studies using doses up to 0.3 mmol/kg and no clinical consequences related to increasing dose have been observed to date. ProHance can be removed by hemodialysis [see Use in Specific Populations (8.6) and Clinical Pharmacology (12.3)].

11 DESCRIPTION

ProHance, a gadolinium-based paramagnetic MRI contrast agent, is a colorless to slightly yellow aqueous, sterile, nonpyrogenic injectable solution. Each mL contains 279.3 mg (0.5 mmol/mL) gadoteridol, 0.23 mg calteridol calcium, 1.21 mg tromethamine and water for injection; pH adjusted with hydrochloric acid and/or sodium hydroxide. ProHance contains no antimicrobial preservative.

Gadoteridol is the gadolinium complex of 10-(2-hydroxy-propyl)-1,4,7,10- tetraazacyclododecane-1,4,7-triacetic acid with a molecular weight of 558.7, an empirical formula of C17H29N4O7Gd and has the following structural formula:

ProHance has a pH of 6.5 to 8.0. Pertinent physiochemical parameters are provided below:

Osmolality | 630 mOsmol/kg water at 37 °C
Viscosity | 1.3 cP at 37 °C
Density | 1.137 g/mL at 25 °C

ProHance has an osmolality that is 2.2 times that of plasma (285 mOsmol/kg water) and is hypertonic under conditions of use.

12 CLINICAL PHARMACOLOGY

12.1 Mechanism of Action

Gadoteridol is a paramagnetic agent and, as such, develops a magnetic moment when placed in a magnetic field. The relatively large magnetic moment produced by the paramagnetic agent results in a relatively large local magnetic field, which can enhance the relaxation rates of water protons in the vicinity of the paramagnetic agent.

In MRI, visualization of normal and pathologic brain tissue depends, in part, on variations in the radiofrequency signal intensity that occur with: 1) differences in proton density; 2) differences of the spin-lattice or longitudinal relaxation times (T1); and 3) differences in the spin-spin or transverse relaxation time (T2). When placed in a magnetic field, gadoteridol decreases T1 relaxation times in the target tissues. At recommended doses, the effect is observed with greatest sensitivity in the T1-weighted sequences.

12.2 Pharmacodynamics

Gadoteridol affects proton relaxation times and consequently the MR signal. Signal intensity is affected by the dose and relaxivity of the gadoteridol molecule. Consistently, for all gadolinium based contrast agents, the relaxivity of gadoteridol decreases with the increase of the magnetic field strength used in clinical MRI (0.2 – 3.0T).

Disruption of the blood-brain barrier or abnormal vascularity allows accumulation of gadoteridol in lesions such as neoplasms, abscesses, and subacute infarcts. The pharmacokinetics of gadoteridol in various lesions is not known.

12.3 Pharmacokinetics

The pharmacokinetics of intravenously administered gadoteridol in normal subjects conforms to a two-compartment open model.

Distribution
After intravenous administration, gadoteridol is rapidly distributed in the extracellular space. The plasma distribution volume (mean ± SD) for the non-renally impaired adults was 0.205 ± 0.025 L/kg. It is unknown if protein binding of gadoteridol occurs in vivo.

Following GBCA administration, gadolinium is present for months or years in brain, bone, skin, and other organs [see Warnings and Precautions (5.4)].

Metabolism
It is unknown if biotransformation or decomposition of gadoteridol occur in vivo.

Elimination
Gadoteridol is eliminated unchanged via the kidneys. The elimination half-life (mean ± SD) is about 1.57 ± 0.08 hours. Within 24 hours post-injection, 94.4 ± 4.8% of the dose is excreted in the urine. The renal and plasma clearance rates (1.41 ± 0.33 mL/ min/kg and 1.50 ± 0.35 mL/ min/kg, respectively) of gadoteridol are essentially identical, indicating no alteration in elimination kinetics on passage through the kidneys and that the drug is essentially cleared through the kidney. The volume of distribution (204 ± 58 mL/kg) is equal to that of extracellular water, and clearance is similar to that of substances which are subject to glomerular filtration.

Specific Populations
Gender
Gender has no clinically relevant effect on the pharmacokinetics of gadoteridol.

Geriatric
There were 7 elderly subjects receiving 0.1 (n = 3) and 0.3 mmol/kg (n = 4) dose of ProHance. The clearance was slightly lower in elderly subjects as compared to non-elderly subjects [see Use in Specific Populations (8.5)].

Pediatric
A population pharmacokinetic analysis incorporated data from 79 subjects, 45 males and 34 females. Among 79 subjects, 41 were healthy subjects including 28 pediatric subjects between 5 years and 15 years of age. The pediatric subjects received a single intravenous dose of 0.1 mmol/kg of ProHance. From population PK model, the mean Cmax was 0.66 ± 0.21 mmol/L in pediatric subjects 2 years to 6 years of age, 0.58 ± 0.06 mmol/L in pediatric subjects 6 years to 12 years of age, and 0.68 ± 0.12 mmol/L in adolescent subjects older than 12 years. The mean AUC0-∞ was 0.74 ± 0.20 mmol/L⋅h in pediatric subjects 2 years to 6 years of age, 0.74 ± 0.09 mmol/L⋅h in pediatric subjects 6 years to 12 years of age, and 0.98 ± 0.09 mmol/L⋅h in adolescent subjects older than 12 years of age. The mean distribution half-life (t1/2,alpha) was 0.14 ± 0.04 hours in pediatric subjects 2 years to 6 years of age, 0.18 ± 0.07 hours in pediatric subjects 6 years to 12 years of age, and 0.20 ± 0.07 hours in adolescent subjects older than 12 years of age. The mean elimination half-life (t1/2,beta) was 1.32 ± 0.006 hours in pediatric subjects 2 years to 6 years, 1.32 ± 0.07 hours in pediatric subjects 6 years to 12 years of age, and 1.61 ± 0.19 hours in adolescent subjects older than 12 years of age. There was no significant gender-related difference in the pharmacokinetic parameters in the pediatric patients. Over 80% of the dose was recovered in urine for pediatric subjects after 10 hours. Pharmacokinetic simulations indicate similar half-life, AUC, and Cmax values for ProHance in pediatric subjects less than 2 years of age when compared to those reported for adults; no age-based dose adjustment is necessary for this pediatric population.

Renal Impairment
In patients with impaired renal function, the serum half-life of gadoteridol is prolonged. After intravenous injection of 0.1 mmol/kg, the elimination half-life of gadoteridol was 10.65 ± 0.06 hours in mild to moderately impaired patients (creatinine clearance 30 to 60 mL/min) and 9.10±0.26 hours in severely impaired patients not on dialysis (creatinine clearance 10 to 30 mL/min). The mean serum clearance of gadoteridol in patients with normal renal function was 116.14 ± 26.77 mL/min, compared to 37.2 ± 16.4 mL/min in patients with mild to moderate renal impairment and 16.0 ± 3.0 mL/min in patients with severe renal impairment.

In patients with moderately and severely impaired renal function about 97% and 76% of the administered dose was recovered in the urine within 7 days and 14 days, respectively.

For patients receiving hemodialysis, physicians may consider the prompt initiation of hemodialysis following the administration of ProHance in order to enhance the contrast agent’s elimination. Seventy- two percent (72%) of gadoteridol is removed from the body after the first dialysis, 91% after the second dialysis, and 98% after the third dialysis session. [See Warnings and Precautions (5.2) and Use in Specific Populations (8.6).]

13 NONCLINICAL TOXICOLOGY

13.1 Carcinogenesis, Mutagenesis, Impairment of Fertility

No animal studies have been performed to evaluate the carcinogenic potential of gadoteridol.

No changes in reproductive performance and outcome of pregnancy were caused in rats and rabbits by daily intravenous administration of ProHance to parent animals before and during gestation up to 1.5 mmol/kg/day (15 times the recommended human dose).

Gadoteridol did not demonstrate genotoxic activity in: bacterial reverse mutation assays using Salmonella typhimurium and Escherichia coli; a mouse lymphoma forward mutation assay; an in vitro cytogenetic assay measuring chromosomal aberration frequencies in Chinese hamster ovary cells; and an in vivo mouse micronucleus assay at intravenous doses up to 5.0 mmol/kg.

14 CLINICAL STUDIES

14.1 MRI of the CNS

ProHance was evaluated in two multicenter trials of 310 evaluable patients suspected of having neurological pathology. After the administration of ProHance 0.1 mmol/kg IV, the results were similar to those described below [see Clinical Studies (14.2)].

In another multicenter study of 49 evaluable adult patients with known intracranial tumor with high suspicion of having cerebral metastases, two doses of ProHance were administered. First ProHance 0.1 mmol/kg was injected followed 30 minutes later with 0.2 mmol/kg. In comparison to the 0.1 mmol/kg dose alone, the addition of the 0.2 mmol/kg dose improved visualization in 67% and improved border definition in 56% of patients. In comparison to non-contrast MRI, the number of lesions after 0.1 mmol/kg increased in 34% of patients. After ProHance 0.2 mmol/kg, this increased to 44%.

Pediatric Patients
ProHance was evaluated in a multicenter study of 103 patients undergoing brain or spine MRI. Among these patients, the age range was 2 to 20 years; 54 were between 2 and 12 years of age; 74% were Caucasian, 11% Black, 12% Hispanic, 2% Asian, and 2% other. ProHance was given in one single 0.1 mmol/kg dose. Repeat dosing was not studied. The results of the non-contrast and ProHance MRI scans were compared. In this database, MRI enhancement was noted in approximately 60% of the scans and additional diagnostic information in 30 to 95% of the scans.

A prospectively planned study of 125 pediatric patients younger than 2 years of age retrospectively selected was performed. These patients (70 boys and 55 girls) had an age range of 1 day to 24 months old; 17 were less than 1 month of age, 40 were between 1 month and 6 months of age, 29 were between 6 months and 12 months of age, and 39 were between 12 months and 24 months of age; 56% were Caucasian, 25% Black, 5% Asian, and 14% other. ProHance was given in one single 0.1 mmol/kg dose. Repeat dosing was not studied. Three independent, blinded readers evaluated pre-contrast MRI image sets and paired pre-plus-post-contrast MRI image sets using ProHance and rated the images according to three co-primary visualization endpoints: lesion border delineation, visualization of lesion internal morphology, and lesion contrast enhancement. All three blinded readers reported improvement in the paired image sets for each of the three co-primary endpoints.

14.2 MRI of the Head and Neck

ProHance was evaluated in two blinded read studies in a total of 133 adults who had an indication for head and neck extracranial or extraspinal MRI. These 133 adults (74 men, 59 women) had a mean age of 53 with a range of 19 to 76 years. Of these patients, 85% were Caucasian, 13% Black, 2% Asian, and less than 1% other. The results of the non-contrast and contrast MRI scans were compared. Approximately 75-82% of the scans were enhanced, 45-48% of the scans provided additional diagnostic information, and 8-25% of the diagnoses were changed. The relevance of the findings to disease sensitivity and specificity has not been fully evaluated.

16 HOW SUPPLIED/STORAGE AND HANDLING

How Supplied
ProHance is supplied as a sterile, nonpyrogenic, and colorless to slightly yellow solution containing 279.3 mg/mL (0.5 mmol/mL) of gadoteridol in single-dose rubber stoppered vials or prefilled syringes; ProHance is available in boxes of:

Five 5 mL fills in single dose 15 mL vials (NDC 0270-1111-04)
Five 10 mL fills in single dose 30 mL vials (NDC 0270-1111-01)
Five 15 mL fills in single dose 30 mL vials (NDC 0270-1111-02)
Five 20 mL fills in single dose 30 mL vials (NDC 0270-1111-03)

Storage and Handling
Store at 25°C (77° F). Excursions permitted to 15°C to 30°C (59°F to 86°F) [See USP Controlled Room Temperature]. Protect from light. DO NOT FREEZE. Should freezing occur in the vial, ProHance should be brought to room temperature before use. If allowed to stand at room temperature for a minimum of 60 minutes, ProHance should return to a clear, colorless to slightly yellow solution. Before use, examine the product to assure that all solids are redissolved and that the container and closure have not been damaged. Should solids persist, discard vial.

17 PATIENT COUNSELING INFORMATION

Medication Guide

- Advise the patient to read the FDA-approved patient labeling (Medication Guide) found at www.prohancemedicationguide.com.

Nephrogenic Systemic Fibrosis
Instruct patients to inform their physician if they:

- have a history of kidney disease
- have recently received a GBCA

GBCAs increase the risk for NSF in patients with impaired elimination of the drugs. To counsel patients at risk for NSF:

- describe the clinical manifestations of NSF
- describe procedures to screen for the detection of renal impairment

Instruct patients to contact their physician if they develop signs or symptoms of NSF following ProHance administration, such as burning, itching, swelling, scaling, hardening and tightening of the skin; red or dark patches on the skin; stiffness in joints with trouble moving, bending or straightening the arms, hands, legs or feet; pain in the hip bones or ribs; or muscle weakness.

General Precautions

- Pregnancy: Advise a pregnant woman of the potential risk of fetal exposure to ProHance [see Use in Specific Populations (8.1)]
- Gadolinium retention: Advise patients that gadolinium is retained for months or years in brain, bone, skin, and other organs in patients with normal renal function. The clinical consequences of retention are unknown. Retention depends on multiple factors and is greater following administration of linear GBCAs than following administration of macrocyclic GBCAs [see Warnings and Precautions (5.4)].

Manufactured for:
Bracco Diagnostics Inc.
Princeton, NJ 08540

By BIPSO GmbH
78224 Singen (Germany)

March 2025

CL101A-06

MEDICATION GUIDE
PROHANCE® (prō-ˈhan(t)s)
(Gadoteridol injection)
for intravenous use

What is the most important information I should know about PROHANCE?

- GBCAs like PROHANCE may cause serious side effects including death, coma, encephalopathy, and seizures when it is given intrathecally (injection given into the spinal canal). It is not known if PROHANCE is safe and effective with intrathecal use. PROHANCE is not approved for this use.
- PROHANCE contains a metal called gadolinium. Small amounts of gadolinium can stay in your body including the brain, bones, skin and other parts of your body for a long time (several months to years).
- It is not known how gadolinium may affect you, but so far, studies have not found harmful effects in patients with normal kidneys.
- Rarely, patients have reported pains, tiredness, and skin, muscle or bone ailments for a long time, but these symptoms have not been directly linked to gadolinium.
- There are different GBCAs that can be used for your MRI exam. The amount of gadolinium that stays in the body is different for different gadolinium medicines. Gadolinium stays in the body more after Omniscan or Optimark than after Eovist, Magnevist, or MultiHance. Gadolinium stays in the body the least after Dotarem, Gadavist, or ProHance.
- People who get many doses of gadolinium medicines, women who are pregnant and young children may be at increased risk from gadolinium staying in the body.
- Some people with kidney problems who get gadolinium medicines can develop a condition with severe thickening of the skin, muscles and other organs in the body (nephrogenic systemic fibrosis). Your healthcare provider should screen you to see how well your kidneys are working before you receive PROHANCE.

What is PROHANCE?

- PROHANCE is a prescription medicine called a gadolinium-based contrast agent (GBCA). PROHANCE, like other GBCAs, is used with a magnetic resonance imaging (MRI) scanner.
- An MRI exam with a GBCA, including PROHANCE, helps your doctor to see problems better than an MRI exam without a GBCA.
- Your doctor has reviewed your medical records and has determined that you would benefit from using a GBCA with your MRI exam.

Do not receive PROHANCE if you have had a severe allergic reaction to PROHANCE.

Before receiving PROHANCE, tell your healthcare provider about all your medical conditions, including if you:

- have had any MRI procedures in the past where you received a GBCA. Your healthcare provider may ask you for more information including the dates of these MRI procedures.
- are pregnant or plan to become pregnant. It is not known if PROHANCE can harm your unborn baby. Talk to your healthcare provider about the possible risks to an unborn baby if a GBCA such as PROHANCE is received during pregnancy
- have kidney problems, diabetes, or high blood pressure
- have had an allergic reaction to dyes (contrast agents) including GBCAs

What are the possible side effects of PROHANCE?

- See “What is the most important information I should know about PROHANCE?”
- Allergic reactions. PROHANCE can cause allergic reactions that can sometimes be serious. Your healthcare provider will monitor you closely for symptoms of an allergic reaction.

The most common side effects of PROHANCE include: nausea, distortion of the sense of taste, and headache.
These are not all the possible side effects of PROHANCE.
Call your doctor for medical advice about side effects. You may report side effects to FDA at 1-800-FDA-1088.

General information about the safe and effective use of PROHANCE.
Medicines are sometimes prescribed for purposes other than those listed in a Medication Guide. You can ask your healthcare provider for information about PROHANCE that is written for health professionals.

What are the ingredients in PROHANCE?
Active ingredient: gadoteridol
Inactive ingredients: calteridol calcium, tromethamine
Manufactured by: BIPSO GmbH-78224 Singen (Germany)
Manufactured for: Bracco Diagnostics Inc., Princeton, NJ 08540
For more information, go to www.imaging.bracco.com or call 1-800-257-5181.

This Medication Guide has been approved by the U.S. Food and Drug Administration

Revised: 03/2025

Prohance 5mL Vial label
NDC 0270-1111-04

PACKAGE LABEL

Prohance 5x10 mL Box
NDC: 0270–1111–01